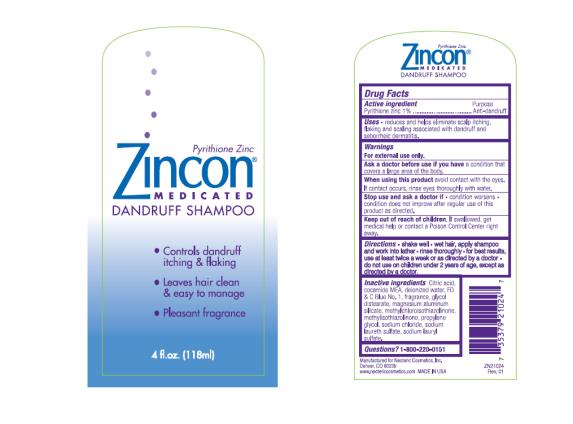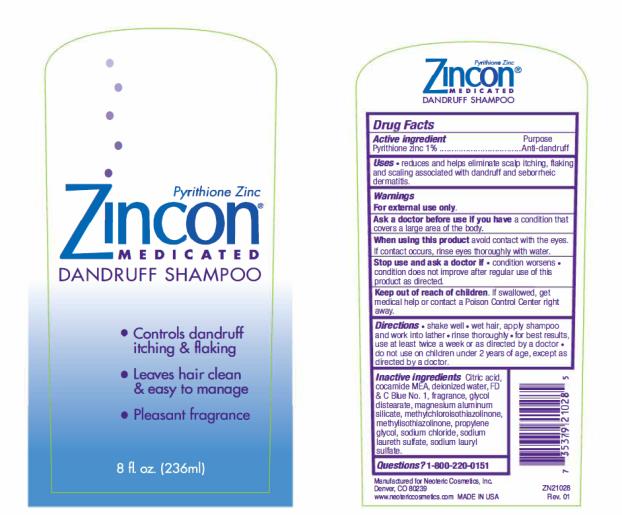 DRUG LABEL: Zincon Medicated Dandruff
NDC: 62673-016 | Form: SHAMPOO
Manufacturer: Neoteric Cosmetics, Inc.
Category: otc | Type: HUMAN OTC DRUG LABEL
Date: 20241007

ACTIVE INGREDIENTS: PYRITHIONE ZINC 0.01 g/1 mL
INACTIVE INGREDIENTS: CITRIC ACID MONOHYDRATE; COCO MONOETHANOLAMIDE; WATER; FD&C BLUE NO. 1; GLYCOL DISTEARATE; MAGNESIUM ALUMINUM SILICATE; METHYLCHLOROISOTHIAZOLINONE; METHYLISOTHIAZOLINONE; PROPYLENE GLYCOL; SODIUM CHLORIDE; SODIUM LAURETH SULFATE; SODIUM LAURYL SULFATE

Zincon Medicated Dandruff Shampoo 4oz

Drug Facts

Active Ingredient

Pyrithione zinc 1%

(To the right)

Purpose

Anti-dandruff

Uses

- Reduces and helps eliminate scalp itching, flaking and scaling associated with dandruff and seborrheic dermatitis.

Warnings:

- For external use only.

Ask a doctor before use if you

have a condition that covers a large area of the body.

When using this product

avoid contact with eyes. If contact occurs, rinse thoroughly with water.

Stop use and ask a doctor if:

- Condition worsens
- Condition does not improve after regular use of this product as directed.

Keep out of reach of children:

- If swallowed, get medical help or contact a Poison Control Center right away.

Directions:

- Shake well
- Wet hair, apply shampoo and work into lather
- Rinse thoroughly
- For best results, use at least twice a week or as directed by a doctor
- Do not use on children under 2 years of age, except as directed by a doctor

Inactive Ingredients

Citric acid, cocamide MEA, deionized water, FD & C Blue No. 1, Fragrance, glycol distearate, magnesium aluminum silicate, methylchloroisothiazolinone, methylisothiazolinone, propylene glycol, sodium chloride, sodium laureth sulfate, sodium lauryl sulfate.

Questions? 1-800-220-0151

Manufactured for Neoteric Cosmetics, Inc.

Denver, CO 80239

WWW. Neotericcosmetics.com MADE IN USA

PRINCIPAL DISPLAY PANEL

Pyrithione Zinc
ZINCON
MEDICATED
DANDRUFF SHAMPOO

- Controls dandruff itching & flaking
- Leaves hair clean & easy to manage
- Pleasant fragrance

4 fl.oz. (118ml)

PRINCIPAL DISPLAY PANEL

Pyrithione Zinc
ZINCON
MEDICATED
DANDRUFF SHAMPOO

- Controls dandruff itching & flaking
- Leaves hair clean & easy to manage
- Pleasant fragrance

8 fl.oz. (236ml)